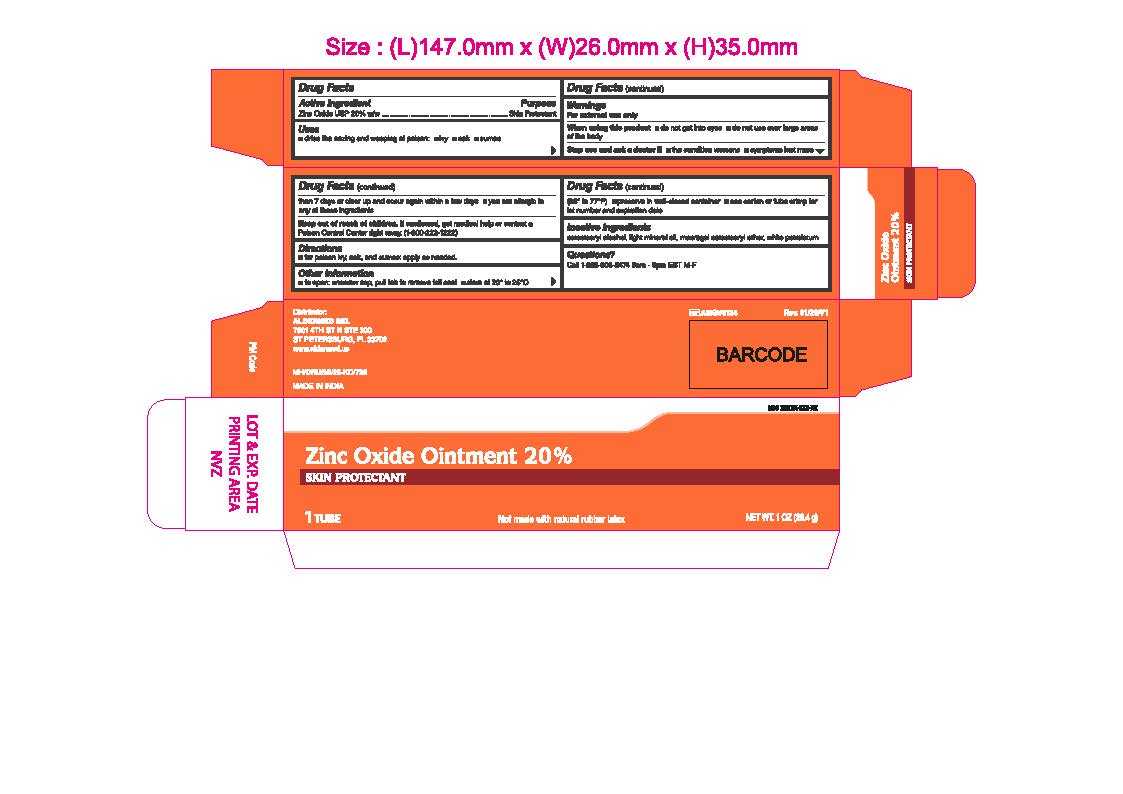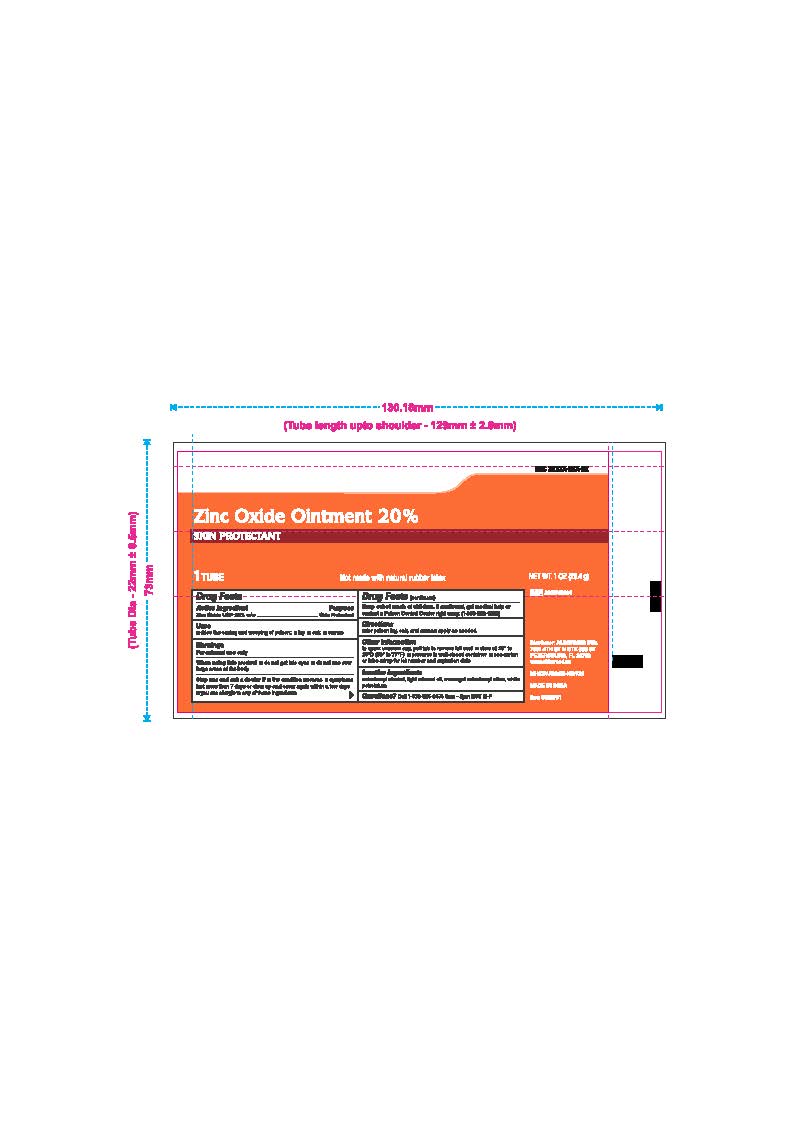 DRUG LABEL: Zinc Oxide
NDC: 87236-007 | Form: OINTMENT
Manufacturer: Aldermed Inc.
Category: otc | Type: HUMAN OTC DRUG LABEL
Date: 20260212

ACTIVE INGREDIENTS: ZINC OXIDE 20 g/100 g
INACTIVE INGREDIENTS: LIGHT MINERAL OIL; CETOSTEARYL ALCOHOL; POLYOXYL 20 CETOSTEARYL ETHER; WHITE PETROLATUM

Zinc Oxide Ointment 20%

Active Ingredient

Zinc Oxide USP 20% w/w

Purpose

Skin Protectant

Uses

• Dries the oozing and weeping of poison: • Ivy • Oak • Sumac

Warnings

For External Use Only

When using this product

• Do not get into eyes

• Do not use over large areas of the body

Stop use and ask a doctor if

• The condition worsens

• Symptoms last more than 7 days or clear up and occur again within a few days

• You are allergic to any of these ingredients

Keep out of reach of children

If swallowed, get medical help or contact a Poison Control Center right away. (1-800-222-1222)

Directions

For poison ivy, oak, and sumac: apply as needed.

Other Information

To open, unscrew cap, pull tab to remove foil seal.

- Store at 20 to 25 C (68 to 77 F)
  - Preserve in well-closed container.
  - See carton ot ube crimp for Lot number and expiration date.

Inactive Ingredients

Cetostearyl Alcohol, Light Mineral Oil, Macrogol Cetostearyl Ether 20, White Petrolatum.

Questions?

Call 1-833-605-84-74 9am-5 pm EST M-F